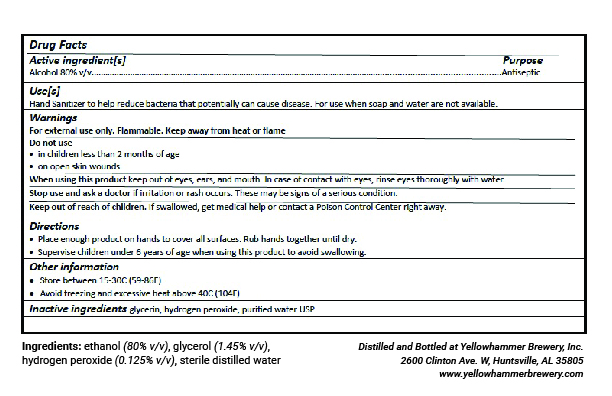 DRUG LABEL: Yellowhammer Brewing Hand Sanitizer
NDC: 74000-819 | Form: LIQUID
Manufacturer: Yellowhammer Brewing, Inc.
Category: otc | Type: HUMAN OTC DRUG LABEL
Date: 20200323

ACTIVE INGREDIENTS: ALCOHOL 80 L/100 L
INACTIVE INGREDIENTS: GLYCERIN; HYDROGEN PEROXIDE; WATER

ACTIVE INGREDIENT

Alcohol 80%

PURPOSE

Antiseptic

INDICATIONS AND USAGE

Hand Sanitizer to help reduce bacteria that potentially can cause disease. For use when soap and water are not available.

WARNINGS

For external use only. Flammable. Keep away from heat or flame.

Do not use:

- in children less than 2 months of age
- on open skin wounds

When using this product, keep out of eyes, ears, and mouth. In case of contact with eyes, rinse eyes thoroughly with water.

Stop use and ask a doctor if irritation or rash occurs. These may be signs of a serious condition.

KEEP OUT OF REACH OF CHILDREN

Keep out of the reach of children. If swallowed, get medical help or contact a Poison Control Center right away.

DOSAGE AND ADMINISTRATION

- Place enough product on hands to cover all surfaces. Rub hands together until dry.
- Supervise children under 6 years of age when using this product to avoid swallowing.

OTHER SAFETY INFORMATION

- Store between 15-30C (59-86F)
- Avoid freezing and excessive heat above 40C (104F)

INACTIVE INGREDIENT

glycerin, hydrogen peroxide, purified water USP